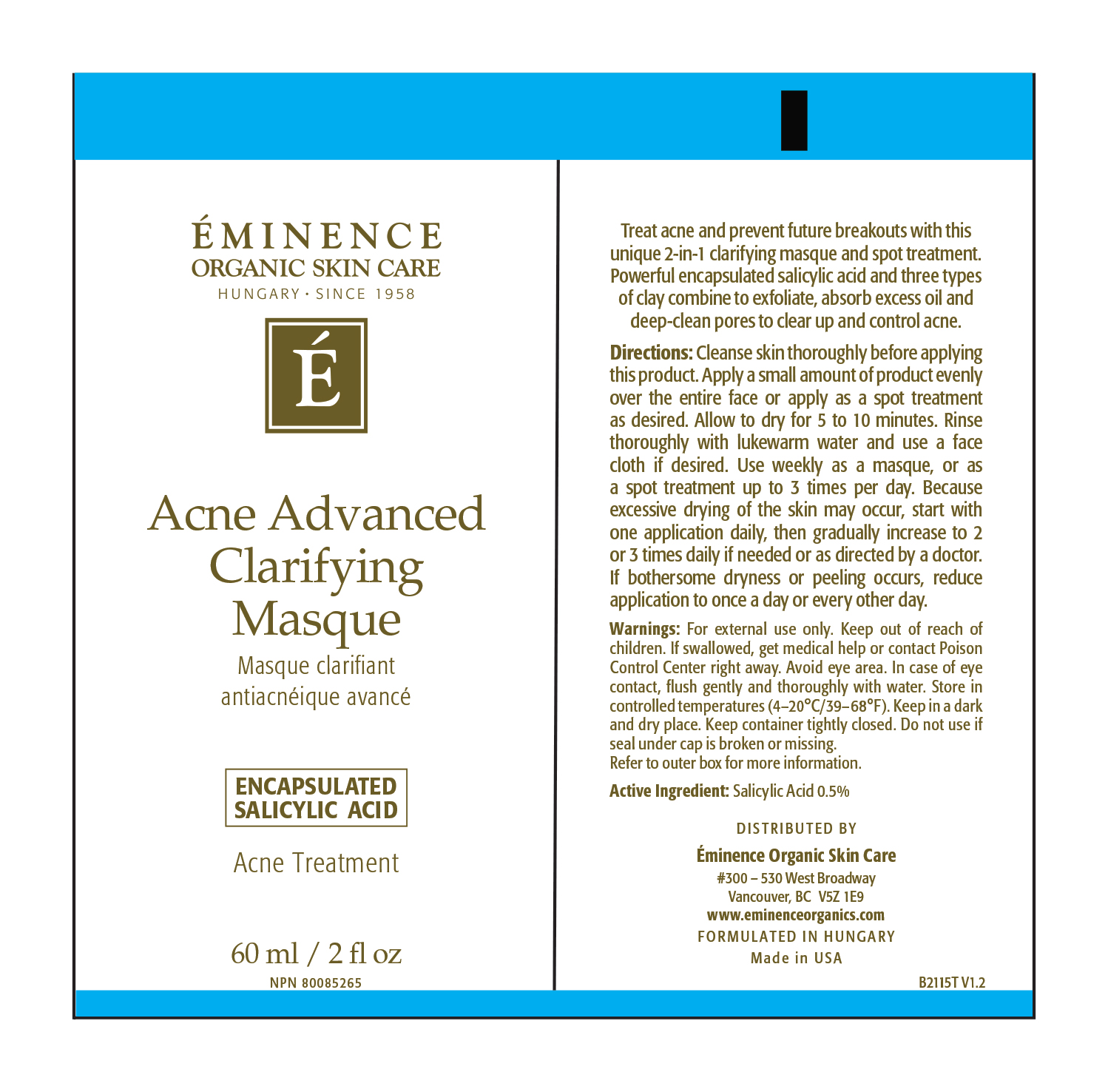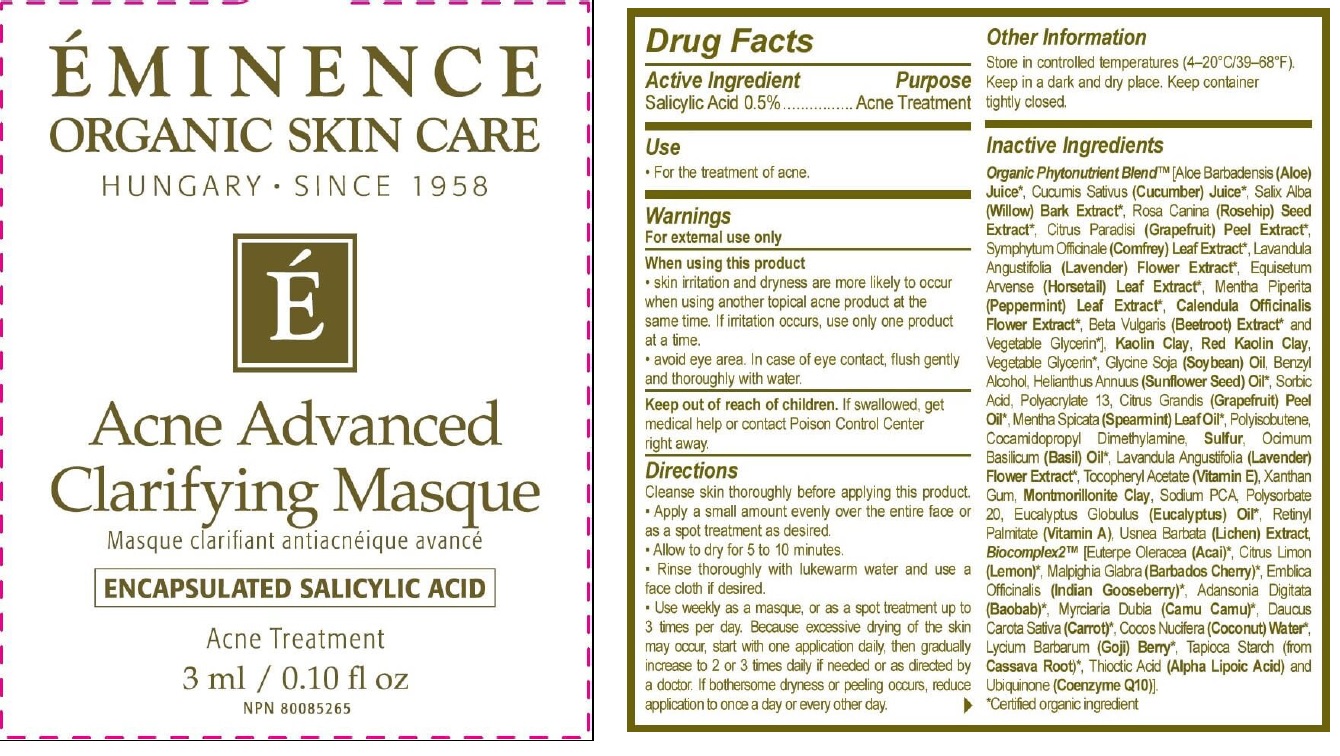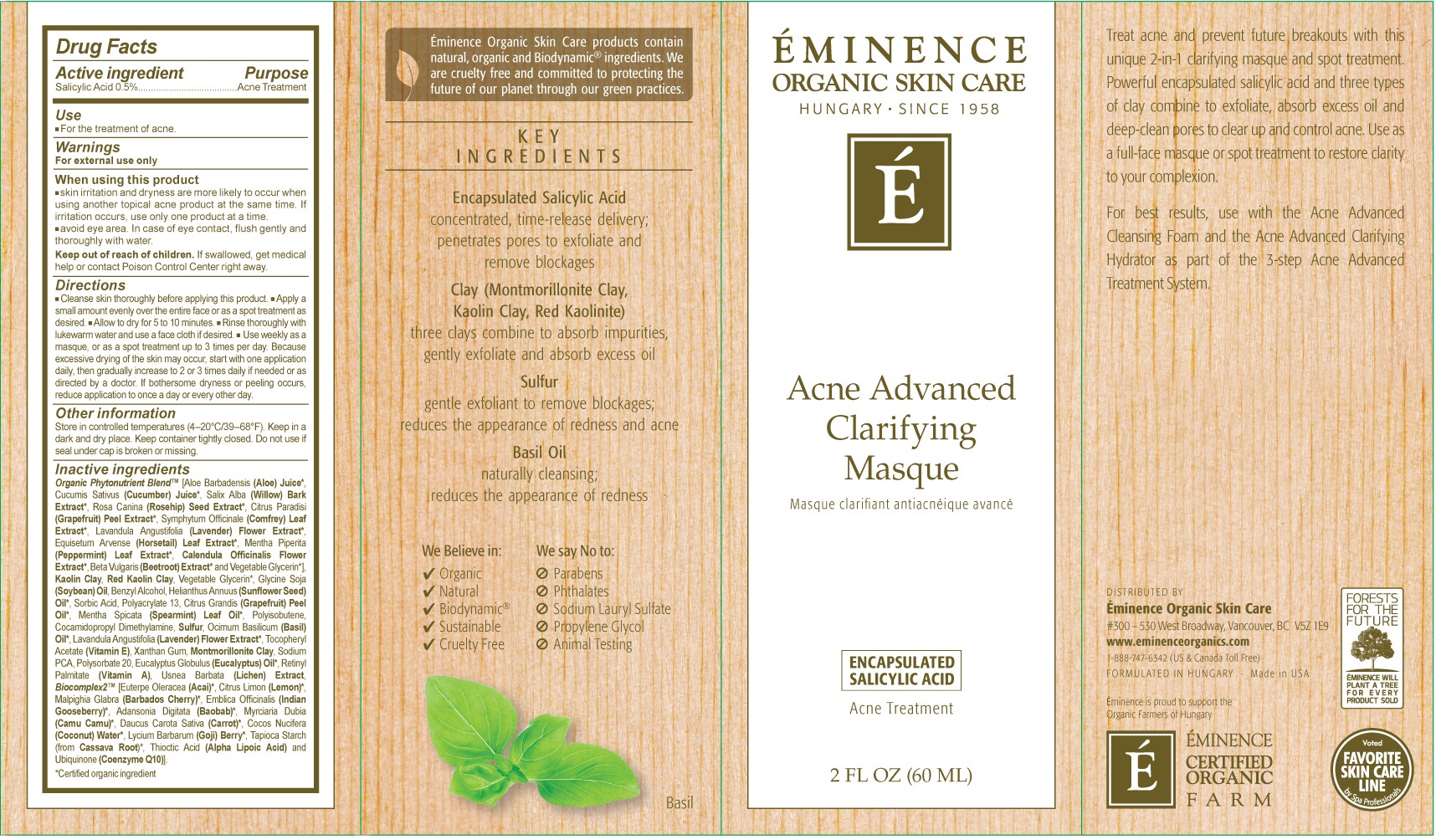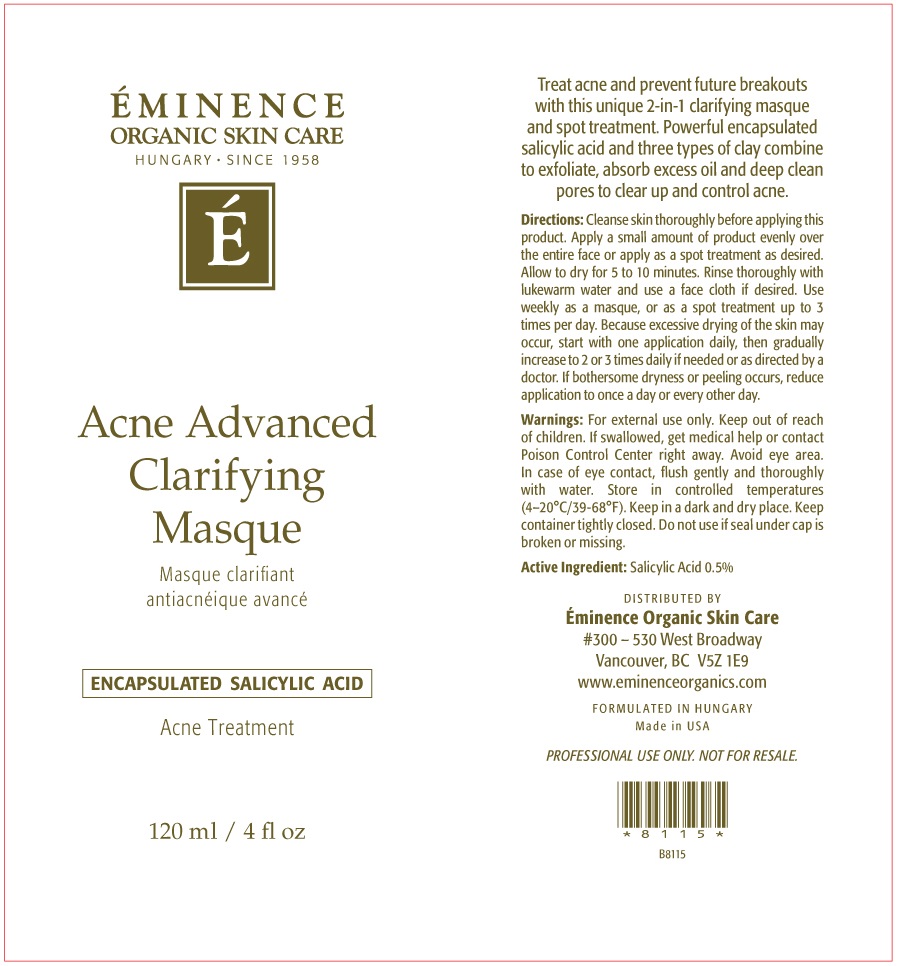 DRUG LABEL: Acne Advanced Clarifying Masque
NDC: 15751-3020 | Form: CREAM
Manufacturer: Eminence Organic Skin Care Ltd.
Category: otc | Type: HUMAN OTC DRUG LABEL
Date: 20231212

ACTIVE INGREDIENTS: SALICYLIC ACID 5 mg/1 mL
INACTIVE INGREDIENTS: ALOE; CUCUMBER; ROSA MOSCHATA OIL; GRAPEFRUIT; SYMPHYTUM UPLANDICUM LEAF; PEPPERMINT; CALENDULA OFFICINALIS FLOWER; BETA VULGARIS; GLYCERIN; SOYBEAN OIL; BENZYL ALCOHOL; SUNFLOWER OIL; SORBIC ACID; SODIUM POLYACRYLATE (2500000 MW); SPEARMINT; COCAMIDOPROPYL DIMETHYLAMINE; SULFUR; BASIL OIL; XANTHAN GUM; MONTMORILLONITE; SODIUM PYRROLIDONE CARBOXYLATE; POLYSORBATE 20; EUCALYPTUS OIL; VITAMIN A PALMITATE; ACAI; CARROT; COCONUT; STARCH, TAPIOCA; THIOCTIC ACID; UBIDECARENONE

Acne Advanced Clarifying Masque

Active ingredient

Salicylic Acid 0.5%

Purpose

Acne Treatment

Use

- For the treatment of acne.

Warnings

For external use only

When using this product

- Skin irritation and dryness are more likely to occur when using another topical acne product at the same time. if irritation occurs, use only one product at a time.
- Avoid eye area. In case of eye contact, flush gently and thoroughly with water.

Keep out of reach of children.

If swallowed, get medical help or contaact Poison Control Center right away.

Direcitons

- Cleanse skin thoroughly before applying this product
- Apply a small amount evenly over the entire face or as a spot treatment as desired.
- Allow to dry for 5 to 10 minutes.
- Rinse thoroughly with lukewarm water and use a face cloth if desired.
- Use weekly as a masque, or as a spot treatment up to 3 times per day. Because excessive drying of the skin may occur, start with one application daily, then gradually increase to 2 ot 3 times daily if needed or as directed by a doctor. if bothersome dryness or peeling occurs, reduce application to once a day or every other day.

Other information

Store in controlled temperatures (4-20°C/39-68°F). Keep in a dark and dry place. Keep container tightly closed. Do not use if seal under cap is broken or missing.

Inactive ingredients

Organic Phytonutrient Blend (Aloe Barbadensis (Aloe) Juice, Cucumis Sativus (Cucumber) Juice, Salix Alba (Willow) Bark Extract, Rosa Canina (Rosehip) Seed Extract, Citrus Paradisi (Grapefruit) Peel Extract, Symphytum Officinale (Comfrey) Leaf Extract, Lavandula Angustifolia (Lavender) Flower Extract, Equisetum Argense (Horsetail Leaf Extract, Mentha Piperita (Peppermint) Leaf Extract, Calendula Officinalis Flower Extract, Beta Vulgaris (Beetroot) Extract and Vegetable Glycerin], Kaolin Clay, Red Kaolin Clay, Vegetable Glycerin, Glycine Soja Soybean) Oil, Benzyl Alcohol, Helianthus Annuus (Sunflower Seed) Oil, Sorbic Acid, Polyacrylate 13, Citrus Grandis (Grapefruit) Peel Oil, Metha Spicata (Spearmint) Leaf Oil, Polysobutene, Cocamidopropyl Dimethylamine, Sulfur, Ocimum Basillicum (Basil) Oil, Lavandula Angustifolia (Lavender) Flower Extract, Tocopheryl Acetate (Vitamin E), Xanthan Gum, Montmorillonite Caly, Sodium PCA, Polysorbate 20, Eucalyptus Globulus (Eucalyptus) Oil, Retinyl Palmitate (Vitamin A), Usnea Barbata (Lichen) Extract, Biocomplex2 [Euterpe Oleracea (Acai), [Euterpe Oleracea (Acai), Citrus Limon (Lemon), Malpighia Glabra (Barbados Cherry), Emblica Officinalis (Indian Gooseberry), Adansonia Digitata (Baobab), Myrciaria Dubia (Camu Camu), Daucus Carota Sativa (Carrot), Cocos Nucifera (Coconut) Water, Lycium Barbarum (Goji) Berry, Tapioca Starch (from Cassave Root), Thioctic Acid (Alpha Lipoic Acid) and Ubiquinone (Coenzyme Q10)

*Certified organic ingredient